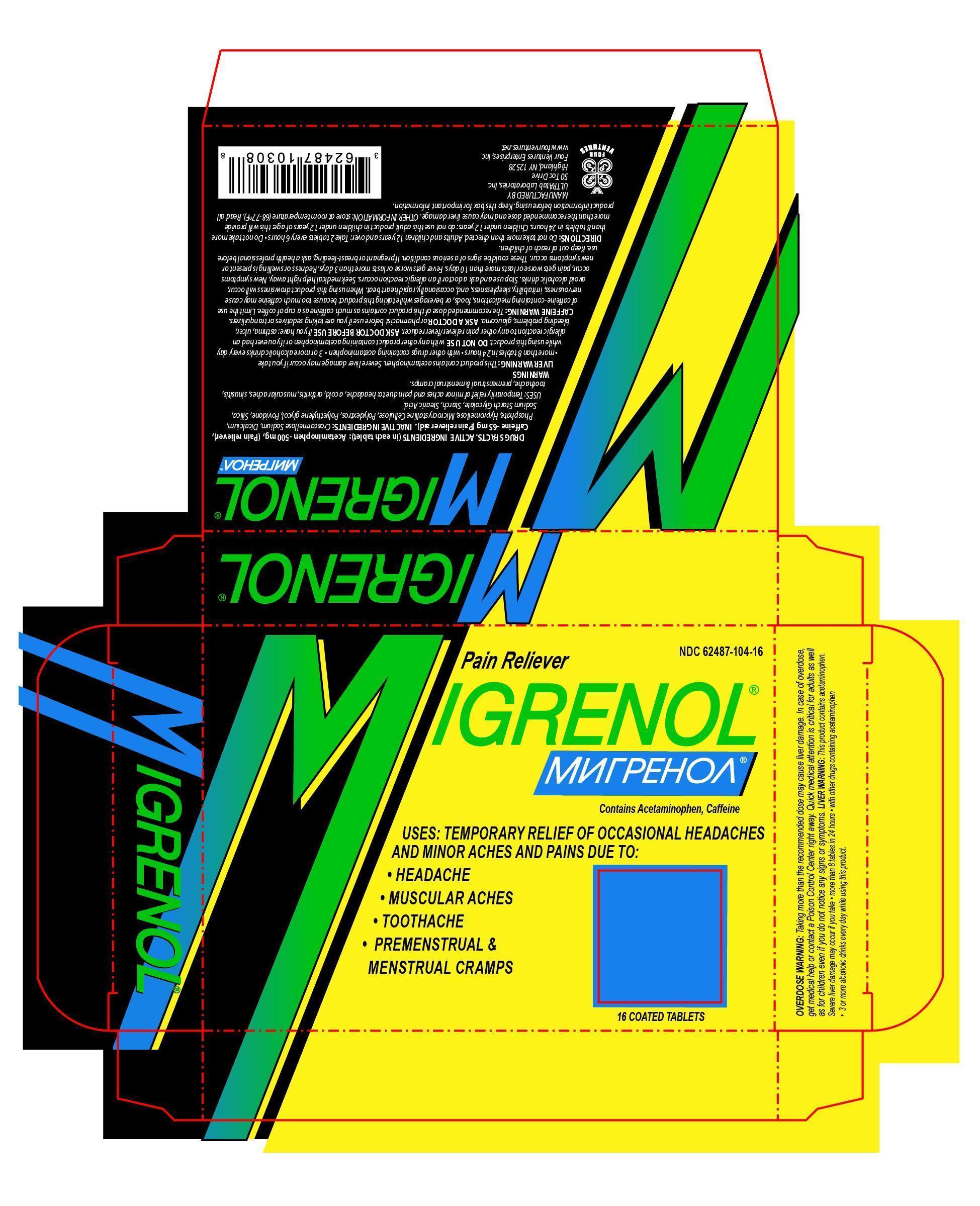 DRUG LABEL: Migrenol
NDC: 69293-565 | Form: TABLET
Manufacturer: Four Ventures Enterprises, Inc.
Category: otc | Type: HUMAN OTC DRUG LABEL
Date: 20181114

ACTIVE INGREDIENTS: ACETAMINOPHEN 500 mg/1 1; CAFFEINE 6 mg/1 1
INACTIVE INGREDIENTS: CELLULOSE, MICROCRYSTALLINE; DIBASIC CALCIUM PHOSPHATE DIHYDRATE; SODIUM STARCH GLYCOLATE TYPE A CORN; SILICON DIOXIDE; CROSCARMELLOSE SODIUM; STEARIC ACID; HYPROMELLOSES; STARCH, CORN

Drug facts

ACTIVE INGREDIENT

Active ingredients (in each tablet): Acetaminophen -500 mg, (Pain reliever),

Caffeine -65 mg (Pain reliever aid).

INDICATIONS AND USAGE

temporary relief of occasional headaches and minor aches and pains due to

headache, muscular aches,

toothache, premenstrual and menstrual cramps

DO NOT USE:

- with any other product containing acetaminophen

- if you ever had an allergic reaction to any other pain reliever/fever reducer.

ASK DOCTOR BEFORE USE if you have liver desease.

ASK A DOCTOR OR PHARMACIST BEFORE USE if you are taking sedatives or tranquilizers when using this product

- drowsiness will occur

- avoid alcoholic drinks

STOP USE AND ASK A DOCTOR IF

- an allergic reaction occurs. Seek medical help right away.

-new symptoms occur

- pain gets worse or lasts more than 10 days

- fever gets worse or lasts more than 3 days

These could be signs of a serious condition.

LIVER WARNING: This product contains acetaminophen.

Severe liver damage may occur if you take

• more than 8 tables in 24 hours

• with other drugs containing acetaminophen

• 3 or more alcoholic drinks every day while using this product.

DOSAGE AND ADMINISTRATION

- do not take more than directed

Adults and children 12 years and over:

- take 2 tablets every 6 hours

- do not take more than 8 tablets in 24 hours

Children under 12 years: do not use this adult product in children under 12 years of age: this will provide more than the recommended dose

and may cause liver damage.

PREGNANCY OR BREAST FEEDING

IF PREGNANT OR BREAST-FEEDING, ask a health professional before use.

Keep out of reach of children.

INACTIVE INGREDIENTS: Croscarmellose Sodium, Dicalcium,

Phosphate, Hypromellose, Microcrystalline Cellulose, Polydextrose, Polyethylene glycol, Povidone, Silica,

Sodium Starch Glycolate, Starch, Stearic Acid.

PURPOSE

Pupose: Pain reliever, Fever Reducer